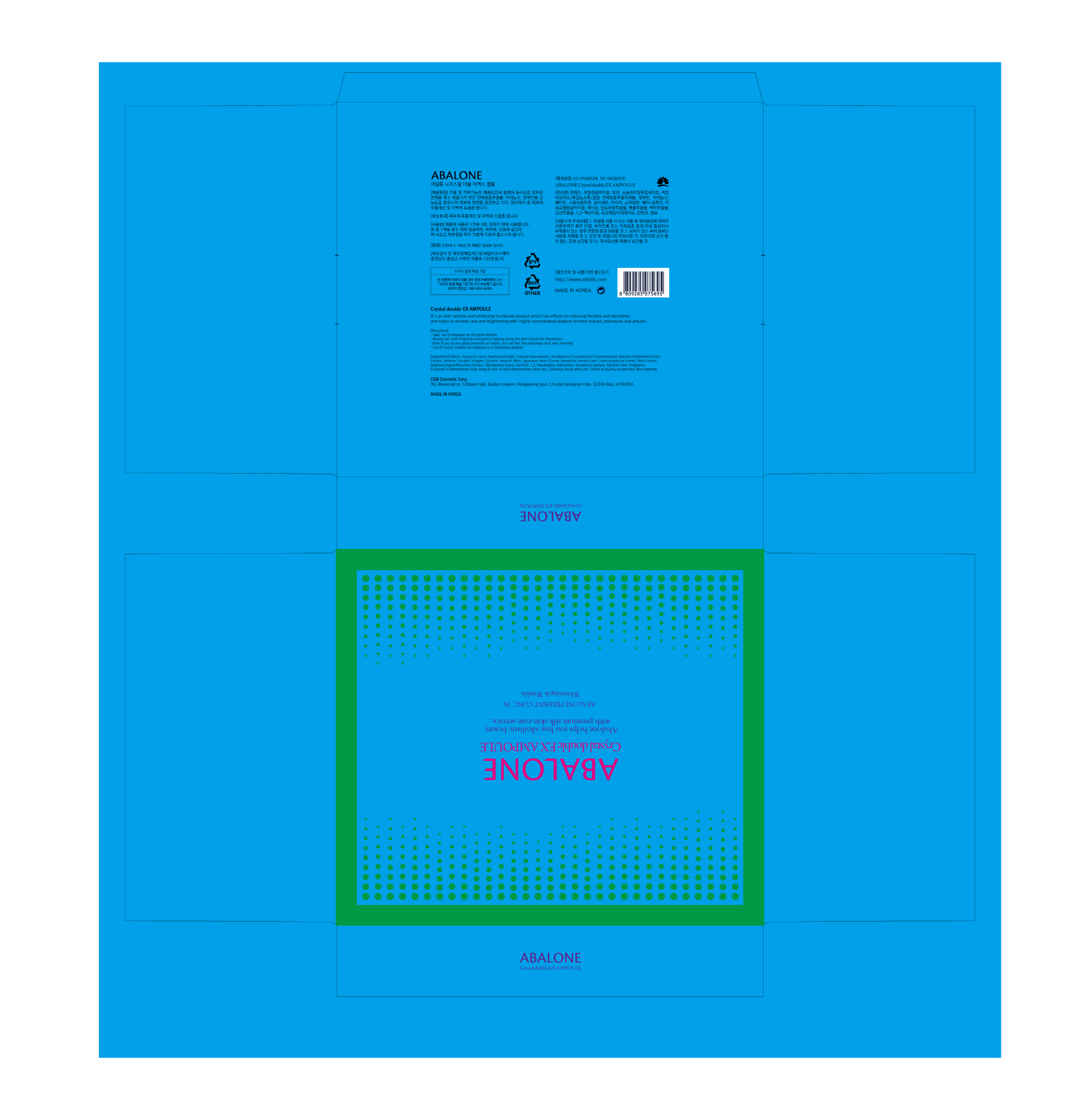 DRUG LABEL: ABALONE CRYSTALDOUBLE EX AMPOULE
NDC: 60611-0006 | Form: LIQUID
Manufacturer: C&BCOSMETIC Co.,Ltd.
Category: otc | Type: HUMAN OTC DRUG LABEL
Date: 20170310

ACTIVE INGREDIENTS: ARBUTIN 2.2 g/100 mL; ADENOSINE 0.044 g/100 mL
INACTIVE INGREDIENTS: GLYCERIN; BUTYLENE GLYCOL; WATER

Drug Facts

ACTIVE INGREDIENT

Arbutin, Adenosine

INACTIVE INGREDIENT

Water, Glycerin, Butylene Glycol, Etc.

PURPOSE

Skin Protectant - Anti-Wrinkle & Whitening

keep out or reach of the children

INDICATIONS AND USAGE

Take 1EA of ampoule on the palm entirely

Mixing well with fingertips and gently tapping along the skin texture for absorption

Even if you do not apply emulsion or cream, you can feel the moistness until next morning

*1EA of crystal Double-EX Ampoule is a throwaway product

WARNINGS

1. Do not use in the following cases(Eczema and scalp wounds)
2.Side Effects
1)Due to the use of this druf if rash, irritation, itching and symptopms of hypersnesitivity occur dicontinue use and consult your phamacisr or doctor
3.General Precautions
1)If in contact with the eyes, wash out thoroughty with water If the symptoms are servere, seek medical advice immediately
2)This product is for exeternal use only. Do not use for internal use
4.Storage and handling precautions
1)If possible, avoid direct sunlight and store in cool and area of low humidity
2)In order to maintain the quality of the product and avoid misuse
3)Avoid placing the product near fire and store out in reach of children

DOSAGE AND ADMINISTRATION

for external use only